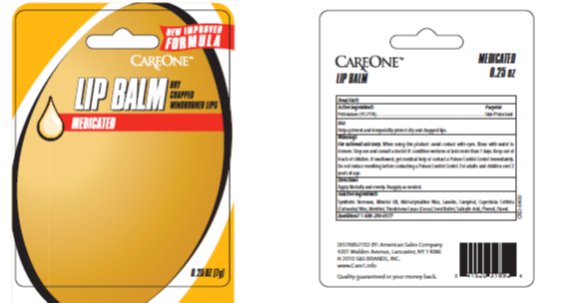 DRUG LABEL: Care One Medicated Lip Balm in a Pot
NDC: 41520-976 | Form: OINTMENT
Manufacturer: American Sales Company
Category: otc | Type: HUMAN OTC DRUG LABEL
Date: 20130311

ACTIVE INGREDIENTS: PETROLATUM 43.75 mg/1 g
INACTIVE INGREDIENTS: WHITE WAX 15.65 mg/1 g; MINERAL OIL 15.5 mg/1 g; MICROCRYSTALLINE WAX 12 mg/1 g; LANOLIN 8 mg/1 g; 3-BROMOCAMPHOR, (+/-)- 1.7 mg/1 g; CARNAUBA WAX .85 mg/1 g; COCOA BUTTER .70 mg/1 g; MENTHOL .70 mg/1 g; 2-BUTANOYLOXYBENZOIC ACID .5 mg/1 g; PHENOL 0.4 mg/1 g

Drug Facts

Active ingredient

Petrolatum

Purpose

Skin Protectant

Keep Out of Reach of Children

If swallowed, get medical help or contact a Poison Control Center immediately. Do not induce vomiting before contacting a Poison Control Center.

Uses

Helps prevent and temporarily protect dry and chapped lips.

Warnings

For external use only: When using this product: avoid contact with eyes. Rinse with water to remove. Stop use and consult a doctor if: condition worsens or lasts more than 7 days. Do not induce vomiting before contacting a Poison Control Center. For adults and children over 2 years of age.

Directions

Apply liberally and evenly. Reapply as needed.

Inactive Ingredients

Synthetic Beeswax, Mineral Oil, Microcrystalline Wax, Lanolin, Camphor, Copernicia Cerifera (Carnauba) Wax, Menthol, Theobroma Cacao (Cocoa) Seed Butter, Salicylic Acid, Phenol, Flavor